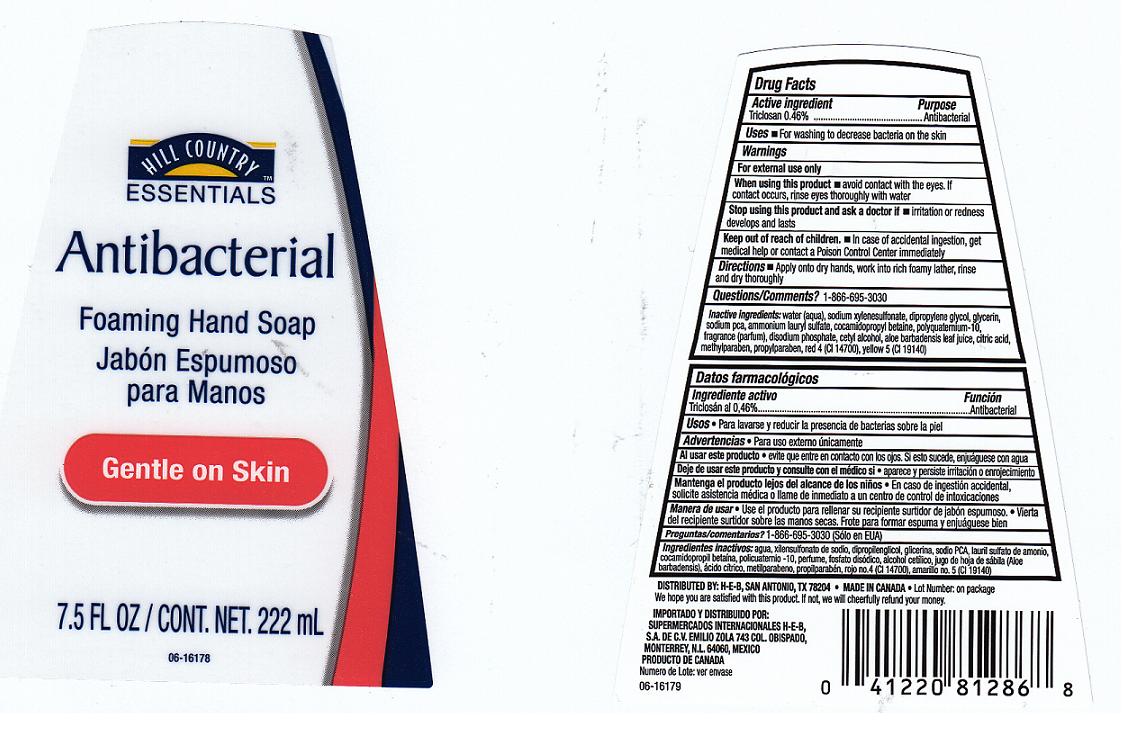 DRUG LABEL: ANTIBACTERIAL FOAMING 
NDC: 37808-177 | Form: LIQUID
Manufacturer: H E B
Category: otc | Type: HUMAN OTC DRUG LABEL
Date: 20110909

ACTIVE INGREDIENTS: TRICLOSAN 0.46 mL/100 mL
INACTIVE INGREDIENTS: WATER; SODIUM  XYLENESULFONATE; DIPROPYLENE GLYCOL; GLYCERIN; SODIUM PYRROLIDONE CARBOXYLATE; AMMONIUM LAURYL SULFATE; COCAMIDOPROPYL BETAINE; POLYQUATERNIUM-10 (400 CPS AT 2%); SODIUM PHOSPHATE, DIBASIC, DIHYDRATE; CETYL ALCOHOL; ALOE VERA LEAF; CITRIC ACID MONOHYDRATE; METHYLPARABEN; PROPYLPARABEN; FD&C RED NO. 4; FD&C YELLOW NO. 5

DRUG FACTS

Active Ingredient

Triclosan 0.46%

Purpose

Antibacterial

Uses

For washing to decrease bacteria on the skin.

Warnings

For external use only.

When using this product

Avoid contact with eyes. If contact occurs, rinse eyes thoroughly with water.

Stop using this product and ask doctor if

Irritation or redness develops and lasts.

Keep out of reach of children

In case of accidental ingestion, get medical help and contact a Poison Control Center immediately.

Directions

Apply onto dry hands, work into rich foamy lather, rinse and dry thoroughly.

Questions or Comments

1-866-695-3030

Inactive Ingredients

WATER, SODIUM XYLENE SULFONATE, DIPROPYLENE GLYCOL, GLYCERIN, SODIUM PCA, AMMONIUM LAURYL SULFATE, COCAMIDOPROPYL BETAINE, POLYQUATERNIUM-10, FRAGRANCE, DISODIUM PHOSPHATE, CETYL ALCOHOL, ALOE BARBADENSIS LEAF JUICE, CITRIC ACID, METHYLPARABEN, PROPYLPARABEN, RED 4 (CI 14700), YELLOW 5 (CI 19140).